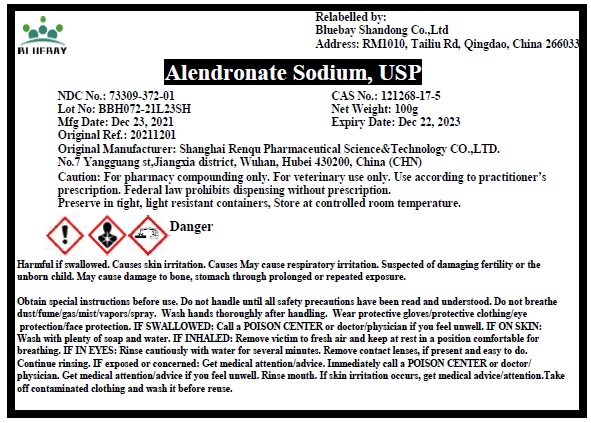 DRUG LABEL: Alendronate Sodium
NDC: 73309-372 | Form: POWDER
Manufacturer: BLUEBAY SHANDONG CO.,LTD
Category: other | Type: BULK INGREDIENT - ANIMAL DRUG
Date: 20220311

ACTIVE INGREDIENTS: ALENDRONATE SODIUM 1 g/1 g

Alendronate Sodium